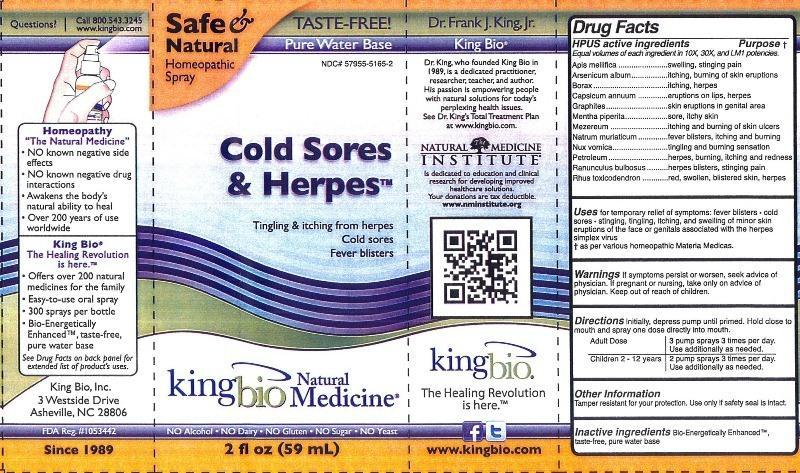 DRUG LABEL: Cold Sores and Herpes
NDC: 57955-5165 | Form: LIQUID
Manufacturer: King Bio Inc.
Category: homeopathic | Type: HUMAN OTC DRUG LABEL
Date: 20120904

ACTIVE INGREDIENTS: APIS MELLIFERA 10 [hp_X]/59 mL; ARSENIC TRIOXIDE 10 [hp_X]/59 mL; SODIUM BORATE 10 [hp_X]/59 mL; CAPSICUM 10 [hp_X]/59 mL; GRAPHITE 10 [hp_X]/59 mL; MENTHA PIPERITA 10 [hp_X]/59 mL; DAPHNE MEZEREUM BARK 10 [hp_X]/59 mL; SODIUM CHLORIDE 10 [hp_X]/59 mL; STRYCHNOS NUX-VOMICA SEED 10 [hp_X]/59 mL; KEROSENE 10 [hp_X]/59 mL; RANUNCULUS BULBOSUS 10 [hp_X]/59 mL; TOXICODENDRON PUBESCENS LEAF 10 [hp_X]/59 mL
INACTIVE INGREDIENTS: WATER

Cold Sores and Herpes

Active Ingredients

HPUS Active ingredients

Equal volumes of each ingredient in 10X, 30X, and LM1 potencies. Apis mellifica, Arsenicum album, Borax, Capsicum annuum, Graphites, Mentha piperita, Mezereum, Natrum muriaticum, Nux vomica, Petroleum, Ranunculus bulbosus, and Rhus toxicodendron.

Inactive Ingredient

Bio-Energetically Enhanced, taste-free, pure water base.

Purpose

HPUS active ingredients Purpose

Apis mellifica............................................Swelling, stinging pain

Arsenicum album......................................itching, burning of skin eruptions

Borax.......................................................itching, herpes

Capsicum annuum....................................eruptions on lips, herpes

Graphites.................................................skin eruptions in genital area

Mentha piperita.........................................sore, itchy skin

Mezereum................................................itching and burning of skin ulcers

Natrum muriaticum....................................fever blisters, itching and burning

Nux vomica..............................................tingling and burning sensation

Petroleum.................................................herpes, burning, itching and redness

Ranunculus bulbosus.................................herpes blisters, stinging pain

Rhus toxicodendron...................................red, swollen, blistered skin, herpes

Warnings

If symptoms persist or worsen, seek advice of physician. If pregnant or nursing, take only on advice of physician. Keep out of reach of children.

Other Information: Tamper resistant for your protection. Use only if safety seal is intact.

Keep out of reach of children.

Directions

Initially, depress pump until primed. Hold close to mouth and spray one dose directly into mouth.

Adult Dose 3 pump sprays 3 times per day. Use additionally as needed.

Children 2-12 years 2 pump sprays 3 times per day. Use additionally as needed.

Indications and Usage

Uses For temporary relief of symptoms: fever blisters, cold sores, stinging, tingling, itching, and swelling of minor skin eruptions of the face or genitals associated with the herpes simplex virus.

As per various homeopathic Materia Medicas.

PACKAGE LABEL

King Bio Inc.

3 Westside Drive

Asheville, NC 28806

Questions? Call 800.543.3245

www.kingbio.com